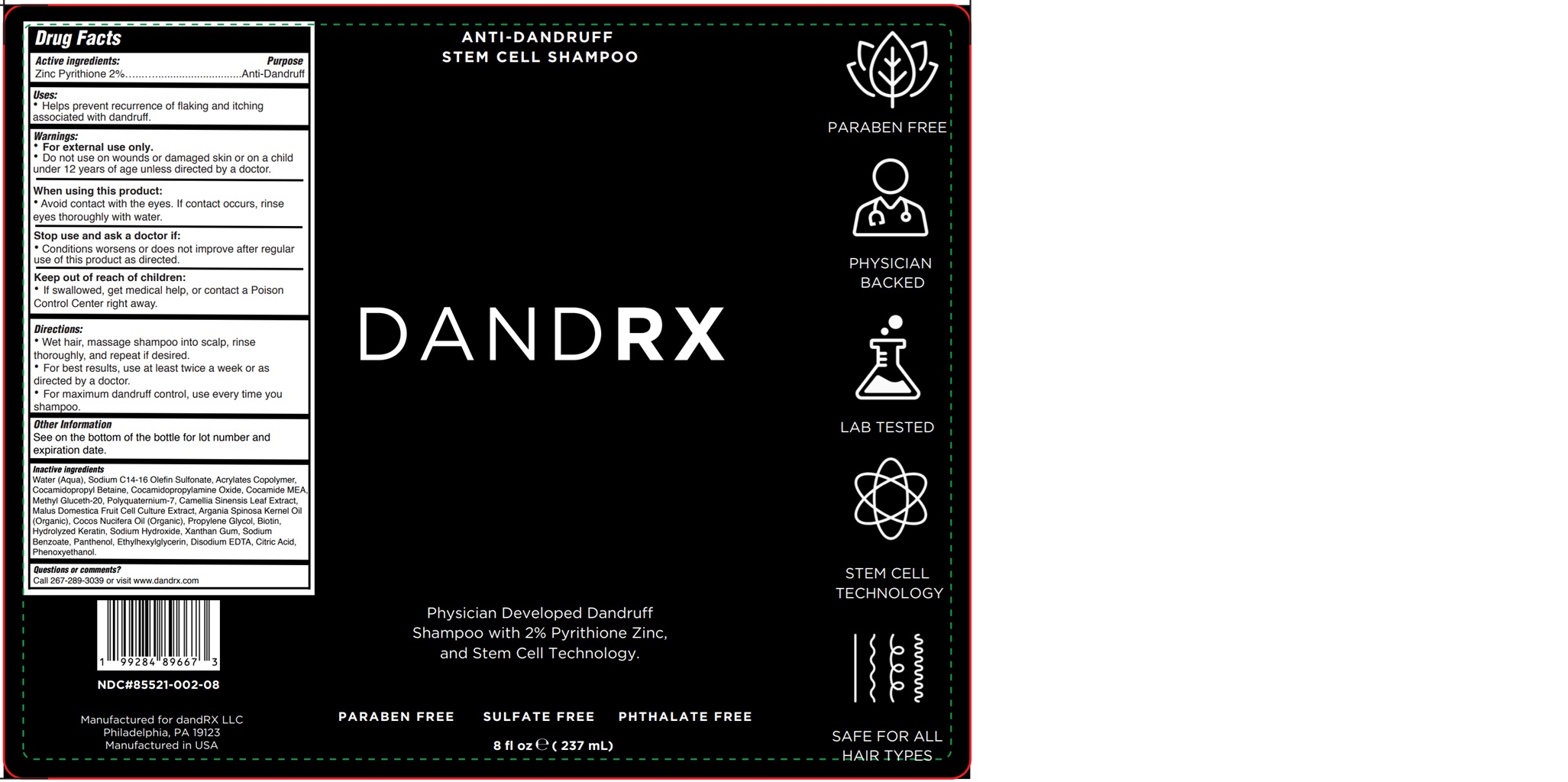 DRUG LABEL: DANDRX ANTI-DANDRUFF
NDC: 85521-002 | Form: SHAMPOO
Manufacturer: dandRX LLC
Category: otc | Type: HUMAN OTC DRUG LABEL
Date: 20250710

ACTIVE INGREDIENTS: PYRITHIONE ZINC 2 g/100 mL
INACTIVE INGREDIENTS: XANTHAN GUM; ETHYLHEXYLGLYCERIN; SODIUM BENZOATE; COCO MONOETHANOLAMIDE; ACRYLATES CROSSPOLYMER-4; ANHYDROUS CITRIC ACID; SODIUM HYDROXIDE; WATER; SODIUM C14-16 OLEFIN SULFONATE; COCAMIDOPROPYLAMINE OXIDE; PHENOXYETHANOL; METHYL GLUCETH-20; CAMELLIA SINENSIS WHOLE; MALUS DOMESTICA WHOLE; ARGAN OIL; PANTHENOL; COCONUT OIL; COCAMIDOPROPYL BETAINE; PROPYLENE GLYCOL; EDETATE DISODIUM; POLYQUATERNIUM-7 (70/30 ACRYLAMIDE/DADMAC; 1600 KD); BIOTIN; HYDROLYZED SHEEP WOOL KERATIN (2000 MW)

85521-002-08

ACTIVE INGREDIENT

Zinc Pyrithione 2%

PURPOSE

Anti-Dandruff

Use

Helps prevent recurrence of flaking and itching associated with dandruff.

WARNINGS

For external use only.

Do not use on wounds or damaged skin or on a child under 12 years of age unless directed by a doctor.

WHEN USING

Avoid contact with the eyes. If contact occurs, rinse eyes thoroughly with water.

STOP USE

Conditions worsens or does not improve after regular use of this product as directed.

KEEP OUT OF REACH OF CHILDREN

If swallowed, get medical help or contact Poison Control Center right away.

Directions

• Wet hair, massage shampoo into scalp, rinse thoroughly, and repeat if desired.

• For best results, use at least twice a week or as directed by a doctor.

• For maximum dandruff control, use every time you shampoo.

OTHER SAFETY INFORMATION

See on the bottom of the bottle for lot number and expiration date.

INACTIVE INGREDIENT

Water (Aqua), Sodium C14-16 Olefin Sulfonate, Acrylates Copolymer, Cocamidopropyl Betaine, Cocamidopropylamine Oxide, Cocamide MEA, Methyl Gluceth-20, Polyquaternium-7, Camellia Sinensis Leaf Extract, Malus Domestica Fruit Cell Culture Extract, Argania Spinosa Kernel Oil (Organic), Cocos Nucifera Oil (Organic), Propylene Glycol, Biotin, Hydrolyzed Keratin, Sodium Hydroxide, Xanthan Gum, Sodium Benzoate, Panthenol, Ethylhexylglycerin, Disodium EDTA, Citric Acid, Phenoxyethanol.

Questions or comments?

Call 267-289-3039 or visit www.dandrx.com